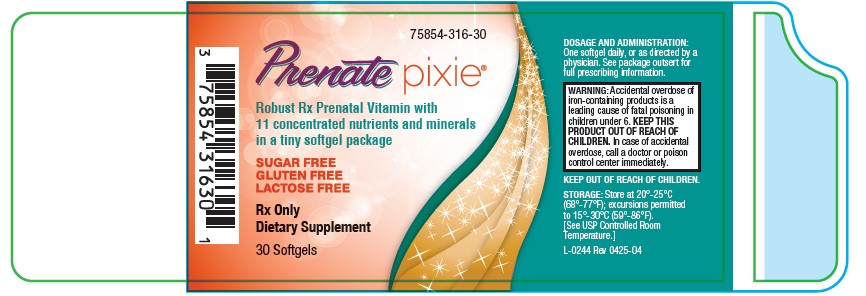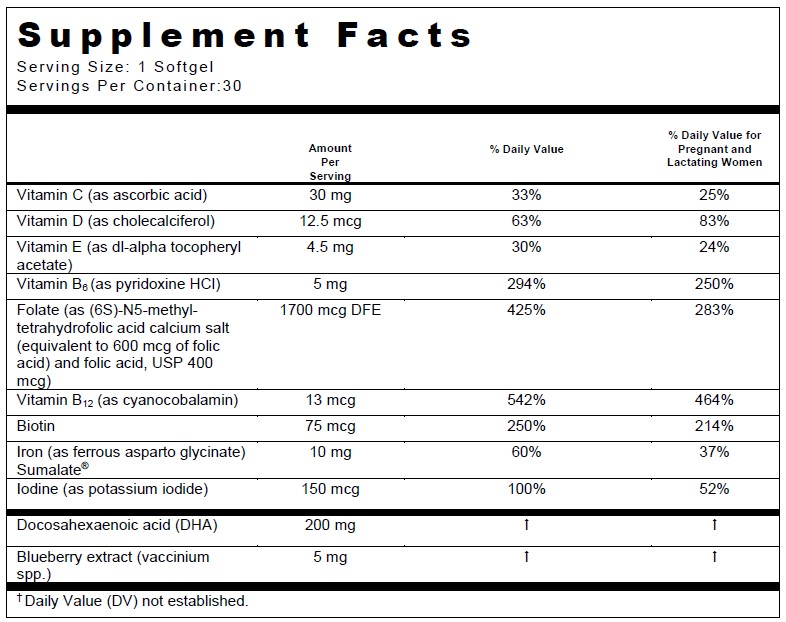 DRUG LABEL: Prenate Pixie
NDC: 75854-316 | Form: TABLET, FILM COATED
Manufacturer: Avion Pharmaceuticals, LLC
Category: prescription | Type: HUMAN PRESCRIPTION DRUG LABEL
Date: 20250514

ACTIVE INGREDIENTS: ASCORBIC ACID 30 mg/1 1; BIOTIN 75 ug/1 1; CHOLECALCIFEROL 12.5 ug/1 1; CYANOCOBALAMIN 13 ug/1 1; FOLIC ACID 400 ug/1 1; FERROUS ASPARTO GLYCINATE 10 mg/1 1; POTASSIUM IODIDE 150 ug/1 1; PYRIDOXINE HYDROCHLORIDE 5 mg/1 1; .ALPHA.-TOCOPHEROL ACETATE, DL- 4.5 mg/1 1; BLUEBERRY 5 mg/1 1; DOCOSAHEXAENOIC ACID 200 mg/1 1; LEVOMEFOLATE CALCIUM 600 ug/1 1
INACTIVE INGREDIENTS: GLYCERIN; LECITHIN, SOYBEAN; WATER; TITANIUM DIOXIDE; FD&C RED NO. 40; CARAMEL; FD&C BLUE NO. 1; GELATIN; BEESWAX; PALM SHORTENING

PRENATE Pixie®75854-0316

DESCRIPTION

Rx Only Dietary Supplement

DESCRIPTION:PRENATE PIXIE®is a prescription prenatal/postnatal multivitamin/mineral/essential fatty acid softgel. Each softgel is purple in color, opaque, and imprinted with “PIX”. Prenate Pixie®contains no ingredient made from gluten-containing grain (wheat, barley, or rye)

INACTIVE INGREDIENT

PRENATE PIXIE®contains fish oil and soy.

OTHER INGREDIENTS: Beeswax, palm shortening and soy lecithin. Capsule (caramel, FD&C blue #1, FD&C red #40, gelatin, glycerin, purified water and titanium dioxide).

INDICATIONS AND USAGE

INDICATIONS:PRENATE PIXIE®is a multivitamin/multimineral fatty acid dietary supplement indicated for use in improving the nutritional status of women throughout pregnancy and in the postnatal period for both lactating and nonlactating mothers.

CONTRAINDICATIONS

CONTRAINDICATIONS:PRENATE PIXIE®is contraindicated in patients with a known hypersensitivity to any of the ingredients.

BOXED WARNING

WARNING:Ingestion of more than 3 grams of omega-3 fatty acids (such as DHA) per day has been shown to have potential antithrombotic effects, including an increased bleeding time and International Normalized Ratio (INR). Administration of omega-3 fatty acids should be avoided in patients taking anticoagulants and in those known to have an inherited or acquired predisposition to bleeding.

PRECAUTIONS

PRECAUTIONS:Folic acid alone is improper therapy in the treatment of pernicious anemia and other megaloblastic anemias where Vitamin B12is deficient. Folic acid in doses above 1.0 mg daily may obscure pernicious anemia in that hematologic remission can occur while neurological manifestations progress.

Biotin levels higher than the recommended daily allowance may cause interference with some laboratory tests, including cardiovascular diagnostic test (e.g. troponin) and hormone tests, and may lead to incorrect test results. Tell your healthcare provider about all prescription and over-the-counter medicines, vitamins, and dietary supplements that you take, including biotin.

BOXED WARNING

WARNING:Accidental overdose of iron-containing products is a leading cause of fatal poisoning in children under 6. KEEP THIS PRODUCT OUT OF REACH OF CHILDREN. In case of accidental overdose, call a doctor or poison control center immediately.

ADVERSE REACTIONS

ADVERSE REACTIONS:Allergic sensitization has been reported following both oral and parenteral administration of folic acid.

DOSAGE AND ADMINISTRATION:Before, during and/or after pregnancy, one softgel daily or as directed by a physician.

HOW SUPPLIED

HOW SUPPLIED:Bottles of 30 softgels (75854-0316-30). The listed product number is not a National Drug Code. Instead, Avion Pharmaceuticals has assigned a product code formatted according to standard industry practice to meet the formatting requirements of pharmacy and healthcare insurance computer systems.

STORAGE AND HANDLING

STORAGE:Store at 20° - 25°C (68° - 77°F); excursions permitted to 15° - 30°C (59° - 86°F) [See USP Controlled Room Temperature.]

THESE STATEMENTS HAVE NOT BEEN EVALUATED BY THE FOOD AND DRUG ADMINISTRATION. THIS PRODUCT IS NOT INTENDED TO DIAGNOSE, TREAT, CURE OR PREVENT ANY DISEASE.

KEEP THIS AND ALL MEDICATIONS OUT OF THE REACH OF CHILDREN.

Sumalate® is a registered trademark of Albion Laboratories, Inc., covered by one or more claims of U.S. Patent Nos. 5,516,925, 6,716,814, 8,007,846, and 8,425,956.

MANUFACTURED FOR:
Avion Pharmaceuticals, LLC
Alpharetta, Georgia 30005
1-888-61-AVION

L-0244 Rev. 0325-03

PACKAGE LABEL

75854-0316-30

Prenate pixie®

Robust Rx Prenatal Vitamin with
11 concentrated nutrients and minerals

in a tiny softgel package

SUGAR FREE

GLUTEN FREE

LACTOSE FREE

Rx Only

Dietary Supplement

30 Softgels